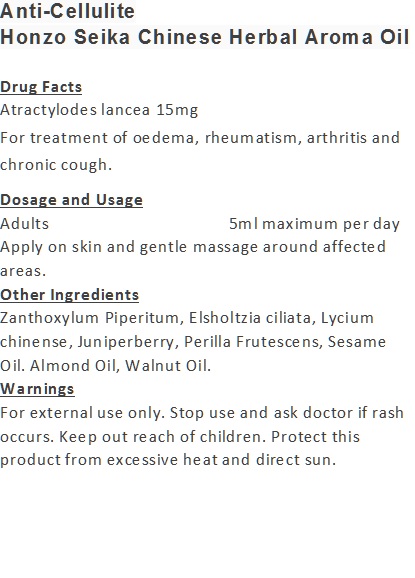 DRUG LABEL: Anti-Cellulite
NDC: 71263-9917 | Form: OIL
Manufacturer: NIC CO., LTD.
Category: otc | Type: HUMAN OTC DRUG LABEL
Date: 20170101

ACTIVE INGREDIENTS: ATRACTYLODES LANCEA ROOT OIL 15 mg/100 mL
INACTIVE INGREDIENTS: ZANTHOXYLUM PIPERITUM WHOLE; WALNUT OIL; LYCIUM CHINENSE WHOLE; JUNIPER BERRY OIL; PERILLA FRUTESCENS LEAF OIL; SESAME OIL; ELSHOLTZIA CILIATA WHOLE; ALMOND OIL

Drug Facts

Atractylodes lancea 15mg

Use

For treatment of oedema, rheumatism, arthritis and chronic cough.

Dosage Suggestion

Adults 5ml maximum per day

INACTIVE INGREDIENT

Other Ingredients

Zanthoxylum Piperitum, Elsholtzia ciliata, Lycium chinense, Juniperberry, Perilla Frutescens, Sesame Oil. Almond Oil, Walnut Oil.

Directions

Apply on skin and gentle massage around affected area.

Warnings

For external use only. Stop use and ask doctor if rash occurs. Keep out reach of children.

Other Information

Protect this product from excessive heat

and direct sun.

Warnings

For external use only. Stop use and ask doctor if rash occurs. Keep out reach of children.